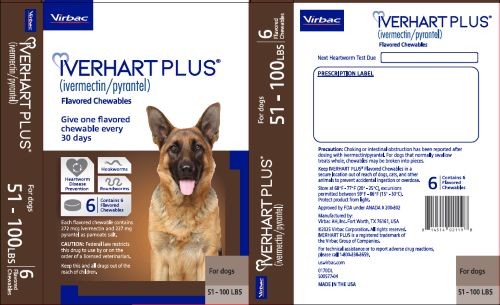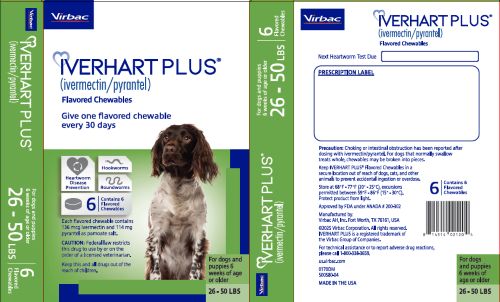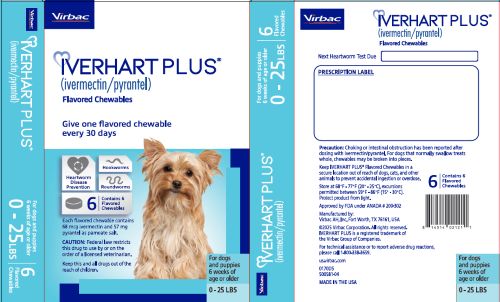 DRUG LABEL: IVERHART PLUS
NDC: 51311-170 | Form: TABLET, CHEWABLE
Manufacturer: Virbac AH, Inc
Category: animal | Type: PRESCRIPTION ANIMAL DRUG LABEL
Date: 20260112

ACTIVE INGREDIENTS: IVERMECTIN 0.068 mg/1 1; PYRANTEL PAMOATE 57 mg/1 1

IVERHART PLUS® (ivermectin/pyrantel) Flavored Chewables

IVERHART PLUS® (ivermectin/pyrantel) Flavored Chewables

CAUTION: Federal law restricts this drug to use by or on the order of a licensed veterinarian.

INDICATIONS AND USAGE

INDICATIONS: For use in dogs to prevent canine heartworm disease by eliminating the tissue stage of heartworm larvae (Dirofilaria immitis) for a month (30 days) after infection and for the treatment and control of roundworms (Toxocara canis, Toxascaris leonina) and hookworms (Ancylostoma caninum, Uncinaria stenocephala, Ancylostoma braziliense).

DOSAGE AND ADMINISTRATION

DOSAGE: IVERHART PLUS® (ivermectin/pyrantel) Flavored Chewables should be administered orally at monthly intervals at the recommended minimum dose level of 6 mcg of ivermectin per kilogram (2.72 mcg/lb) and 5 mg of pyrantel (as pamoate salt) per kg (2.27 mg/lb) of body weight. The recommended dosing schedule for prevention of canine heartworm disease and for the treatment and control of roundworms and hookworms is as follows:

Dog Weight | Flavored Chewable Per Month | Ivermectin Content | Pyrantel Content | Color Coding on Carton
0-25 lbs | 1 | 68 mcg | 57 mg | Blue
26-50 lbs | 1 | 136 mcg | 114 mg | Green
51-100 lbs | 1 | 272 mcg | 227 mg | Brown

IVERHART PLUS Flavored Chewables are recommended for dogs 6 weeks of age and older. For dogs over 100 lbs use the appropriate combination of these flavored chewables.

ADMINISTRATION: Remove only one chewable at a time from the foil-backed blister card. Return the card with the remaining chewables to its box to protect the product from light.

Because most dogs find IVERHART PLUS Flavored Chewables palatable, the product can be ordered to the dog by hand. To avoid the risk of choking or intestinal obstruction, the chewable should be administered in a manner that encourages the dog to chew, rather than to swallow without chewing (see PRECAUTIONS and POST-APPROVAL EXPERIENCE). Chewables may be broken into pieces and fed to dogs that normally swallow treats whole. Alternatively, it may be added intact to a small amount of dog food to encourage chewing, but care should be taken to ensure that the dog consumes the complete dose at one time.

Treated animals should be observed for a few minutes after administration to ensure that part of the dose is not lost or rejected. If it is suspected that any of the dose has been lost, redosing is recommended.

IVERHART PLUS Flavored Chewables should be given at monthly intervals during the period of the year when mosquitoes (vectors), potentially carrying infective heartworm larvae, are active. The initial dose must be given within a month (30 days) after the dogs first exposure to mosquitoes. The final dose must be given within a month (30 days) after the dogs last exposure to mosquitoes.
When replacing another heartworm preventive product in a heartworm disease preventive program, the first dose of IVERHART PLUS Flavored Chewables must be given within a month (30 days) of the last dose of the former medication.

If the interval between doses exceeds a month (30 days), the efficacy of ivermectin can be reduced. Therefore, for optimal performance, the flavored chewable must be given once a month on or about the same day of the month. If treatment is delayed, whether by a few days or many, immediate treatment with IVERHART PLUS Flavored Chewables and resumption of the recommended dosing regimen will minimize the opportunity for the development of adult heartworms.

Monthly treatment with IVERHART PLUS Flavored Chewables also provides effective treatment and control of roundworms (T. canis, T. leonina) and hookworms (A. caninum, U. stenocephala, A. braziliense). Clients should be advised of measures to be taken to prevent reinfection with intestinal parasites.

SUMMARY OF SAFETY AND EFFECTIVENESS

EFFICACY: IVERHART PLUS (ivermectin/pyrantel) Flavored Chewables, given orally using the recommended dose and regimen, are effective against the tissue larval stage of D. immitis for a month (30 days) after infection and, as a result, prevent the development of the adult stage. IVERHART PLUS Flavored Chewables are also effective against canine roundworms (T. canis, T. leonina) and hookworms (A. caninum, U. stenocephala, A. braziliense).

ACCEPTABILITY: In a trial in client-owned dogs, IVERHART PLUS Flavored Chewables were shown to be a palatable oral dosage form consumed at first offering by the majority of dogs.

PRECAUTIONS

PRECAUTIONS: All dogs should be tested for existing heartworm infection before starting treatment with IVERHART PLUS Flavored Chewables, which are not effective against adult D. immitis. Infected dogs must be treated to remove adult heartworms and microfilariae before initiating a program with IVERHART PLUS Flavored Chewables.

While some microfilariae may be killed by the ivermectin in IVERHART PLUS Flavored Chewables at the recommended dose level, IVERHART PLUS Flavored Chewables are not effective for microfilariae clearance. A mild hypersensitivity-type reaction, presumably due to dead or dying microfilariae and particularly involving a transient diarrhea, has been observed in clinical trials with ivermectin alone after treatment of some dogs that have circulating microfilariae.

Choking or intestinal obstruction has been reported after dosing with ivermectin/pyrantel. For dogs that normally swallow treats whole, chewables may be broken into pieces (see POST-APPROVAL EXPERIENCE).

Keep this and all drugs out of the reach of children. In case of ingestion by humans, clients should be advised to contact a physician immediately. Physicians may contact a Poison Control Center for advice concerning cases of ingestion by humans.

Keep IVERHART PLUS Flavored Chewables in a secure location out of reach of dogs, cats, and other animals to prevent accidental ingestion or overdose.

ADVERSE REACTIONS

ADVERSE REACTIONS: In clinical trials with ivermectin/pyrantel, vomiting or diarrhea within 24 hours of dosing was observed (1.1% of administered doses).

POST-APPROVAL EXPERIENCE (2022): The following adverse events are based on post-approval adverse drug experience reporting for ivermectin/pyrantel. Not all adverse events are reported to FDA/CVM. It is not always possible to reliably estimate the adverse event frequency or establish a causal relationship to product exposure using these data.

The following adverse events reported in dogs are listed in decreasing order of reporting frequency:
Vomiting, diarrhea, lethargy, anorexia, seizures, ataxia, muscle tremors, hypersalivation, pruritus. In some cases, choking or intestinal obstruction has been reported after administration of
ivermectin/pyrantel.

CONTACT INFORMATION: To report suspected adverse drug events, for technical assistance, or to obtain a copy of the Safety Data Sheet (SDS), contact Virbac AH, Inc. at 1-800-338-3659. For additional information about adverse drug experience reporting for animal drugs, contact FDA at 1-888-FDA-VETS, or www.fda.gov/reportanimalae.

OTHER SAFETY INFORMATION

SAFETY: Studies with ivermectin indicate that certain dogs of the Collie breed are more sensitive to the effects of ivermectin administered at elevated dose levels (more than 16 times the target use level of 6 mcg/kg) than dogs of other breeds. At elevated doses, sensitive dogs showed adverse reactions which included mydriasis, depression, ataxia, tremors, drooling, paresis, recumbency, excitability, stupor, coma and death. lvermectin demonstrated no signs of toxicity at 10 times the recommended dose (60 mcg/kg) in sensitive Collies. Results of these trials and bioequivalency studies, support the safety of ivermectin products in dogs, including Collies, when used as recommended.

lvermectin/pyrantel has shown a wide margin of safety at the recommended dose level in dogs, including pregnant or breeding bitches, stud dogs and puppies aged 6 or more weeks. In clinical trials, many commonly used flea collars, dips, shampoos, anthelmintics, antibiotics, vaccines and steroid preparations have been administered with ivermectin/pyrantel in a heartworm disease preventive program.

In one trial, where some pups had parvovirus, there was a marginal reduction in efficacy against intestinal nematodes, possibly due to a change in intestinal transit time.

HOW SUPPLIED

HOW SUPPLIED: IVERHART PLUS Flavored Chewables are available in three dosage strengths (See DOSAGE section) for dogs of different weights. Each strength comes in a box of 6 tablets, packed 10 boxes per display box.

STORAGE AND HANDLING

STORAGE INFORMATION: Store at 68°F - 77°F (20° - 25°C), excursions permitted between 59°F - 86°F (15° - 30°C). Protect product from light.

STATEMENT OF IDENTITY

Approved by FDA under ANADA # 200-302

Manufactured by: Virbac AH, Inc.
Fort Worth, TX 76161, USA
301732-08
03/2025

© 2025 Virbac Corporation. All rights reserved.
IVERHART PLUS is a registered trademark of the
Virbac Group of Companies.